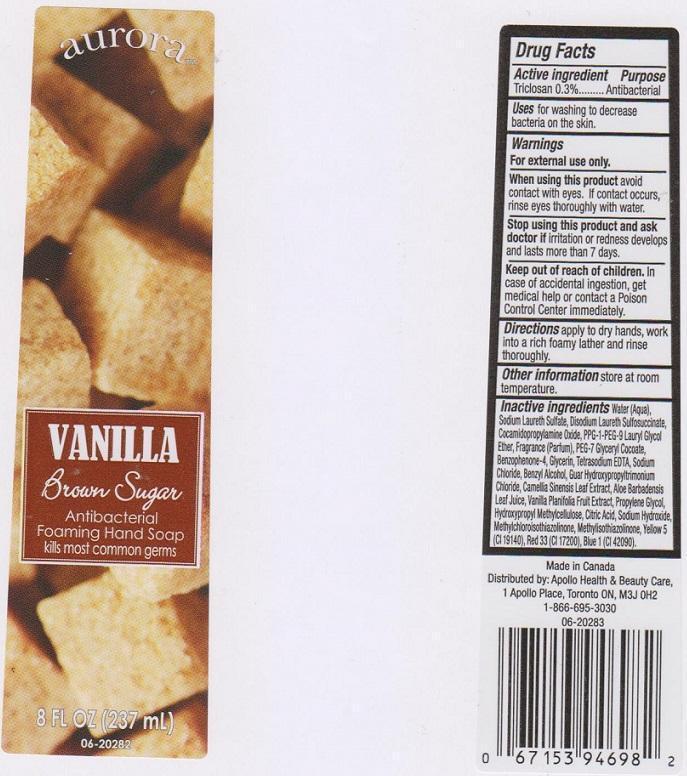 DRUG LABEL: AURORA
NDC: 63148-107 | Form: LIQUID
Manufacturer: APOLLO HEALTH AND BEAUTY CARE
Category: otc | Type: HUMAN OTC DRUG LABEL
Date: 20150115

ACTIVE INGREDIENTS: TRICLOSAN 3 mg/1 mL
INACTIVE INGREDIENTS: WATER; SODIUM LAURETH SULFATE; DISODIUM LAURETH SULFOSUCCINATE; COCAMIDOPROPYLAMINE OXIDE; PPG-1-PEG-9 LAURYL GLYCOL ETHER; PEG-7 GLYCERYL COCOATE; SULISOBENZONE; GLYCERIN; EDETATE SODIUM; SODIUM CHLORIDE; BENZYL ALCOHOL; GUAR HYDROXYPROPYLTRIMONIUM CHLORIDE (1.7 SUBSTITUENTS PER SACCHARIDE); GREEN TEA LEAF; ALOE VERA LEAF; VANILLA; PROPYLENE GLYCOL; HYPROMELLOSES; CITRIC ACID MONOHYDRATE; SODIUM HYDROXIDE; METHYLCHLOROISOTHIAZOLINONE; METHYLISOTHIAZOLINONE; FD&C YELLOW NO. 5; D&C RED NO. 33; FD&C BLUE NO. 1

DRUG FACTS

ACTIVE INGREDIENT

TRICLOSAN 0.3%

PURPOSE

ANTIBACTERIAL

USES

FOR WASHING TO DECREASE BACTERIA ON THE SKIN

WARNINGS

FOR EXTERNAL USE ONLY

WHEN USING THIS PRODUCT

AVOID CONTACT WITH EYES. IF CONTACT OCCURS, RINSE EYES THOROUGHLY WITH WATER

STOP USING THIS PRODUCT AND ASK DOCTOR IF

IRRITATION OR REDNESS DEVELOPS AND LASTS MORE THAN 7 DAYS

KEEP OUT OF REACH OF CHILDREN

IN CASE OF ACCIDENTAL INGESTION, GET MEDICAL HELP OR CONTACT A POISON CONTROL CENTER IMMEDIATELY

DIRECTIONS

APPLY TO DRY HANDS, WORK INTO A RICH FOAMY LATHER AND RINSE THOROUGHLY

OTHER INFORMATION

STORE ST ROOM TEMPERATURE

INACTIVE INGREDIENT

WATER (AQUA), SODIUM LAURETH SULFATE, DISODIUM LAURETH SULFOSUCCINATE, COCAMIDOPROPYLAMINE OXIDE, PPG-1-PEG-9 LAURYL GLYCOL ETHER, FRAGRANCE (PARFUM), PEG-7 GLYCERYL COCOATE, BENZOPHENONE-4, GLYCERIN, TETRASODIUM EDTA, SODIUM CHLORIDE, BENZYL ALCOHOL, GUAR HYDROXYPROPYLTRIMONIUM CHLORIDE, CAMELLIA SINENSIS LEAF EXTRACT, ALOE BARBADENSIS LEAF JUICE, VANILLA PLANIFOLIA FRUIT EXTRACT, PROPYLENE GLYCOL, HYDROXYPROPYL METHYLCELLULOSE, CITRIC ACID, SODIUM HYDROXIDE, METHYCHLOROISOTHIAZOLINONE, METHYLISOTHIAZOLINONE, YELLOW 5 (CI 19140), RED 33 (CI 17200), BLUE 1 (CI 42090)